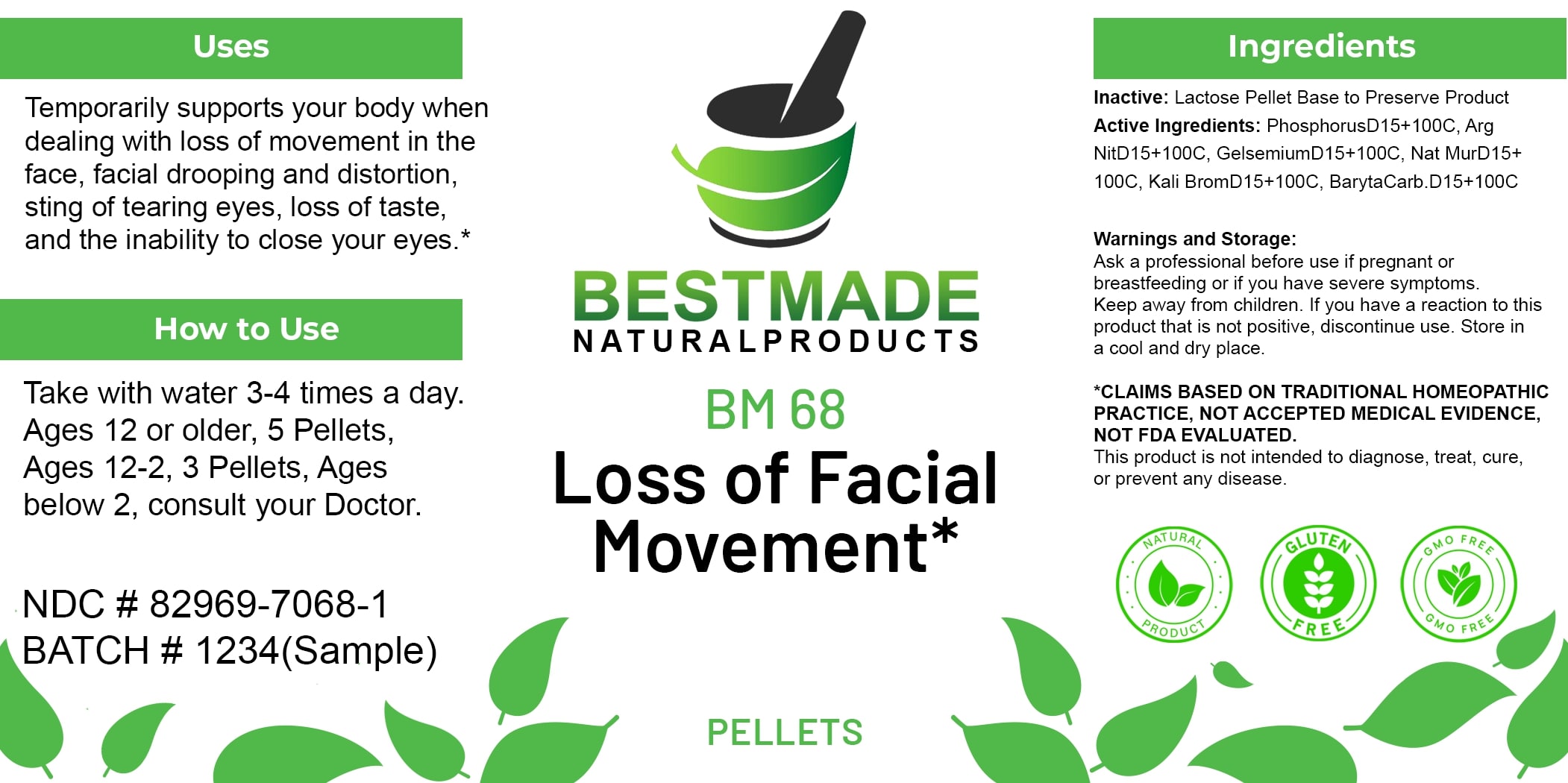 DRUG LABEL: Bestmade Natural Products BM68 Pellets
NDC: 82969-7068 | Form: TABLET, SOLUBLE
Manufacturer: Bestmade Natural Products
Category: homeopathic | Type: HUMAN OTC DRUG LABEL
Date: 20250408

ACTIVE INGREDIENTS: SODIUM CHLORIDE 30 [hp_C]/30 [hp_C]; SILVER NITRATE 30 [hp_C]/30 [hp_C]; GELSEMIUM SEMPERVIRENS ROOT 30 [hp_C]/30 [hp_C]; PHOSPHORUS 30 [hp_C]/30 [hp_C]; POTASSIUM BROMIDE 30 [hp_C]/30 [hp_C]; BARIUM CARBONATE 30 [hp_C]/30 [hp_C]
INACTIVE INGREDIENTS: LACTOSE 30 [hp_C]/30 [hp_C]

BM68 Pellets

DOSAGE AND ADMINISTRATION

How to Use

Take with water 3-4 times a day. Ages 12 or older, 5 Pellets, Ages 12-2, 3 Pellets, Ages below 2, consult your Doctor.

INACTIVE INGREDIENT

Ingredients

Inactive: Lactose Pellet Base to Preserve Product

ACTIVE INGREDIENT

Active Ingredients: PhosphorusD15+100C, Arg NitD15+100C(Argentum Nitricum), GelsemiumD15+100C(Jasmine), Nat MurD15+100C(Natrum Muriaticum), KaliBromD15+100C(Kali Bromatum), Baryta Carb D15+100C(Baryta Carbonica)

Uses

Temporarily supports your body when dealing with loss of movement in the face, facial drooping and distortion, sting of tearing eyes, loss of taste, and the inability to close your eyes.*

*CLAIMS BASED ON TRADITIONAL HOMEOPATHIC PRACTICE. NOT ACCEPTED MEDICAL EVIDENCE. NOT FDA EVALUATED.

This product is not intended to diagnose, treat, cure, or prevent any disease.

Uses

Temporarily supports your body when dealing with loss of movement in the face, facial drooping and distortion, sting of tearing eyes, loss of taste, and the inability to close your eyes.*

*CLAIMS BASED ON TRADITIONAL HOMEOPATHIC PRACTICE. NOT ACCEPTED MEDICAL EVIDENCE. NOT FDA EVALUATED.

This product is not intended to diagnose, treat, cure, or prevent any disease.

KEEP OUT OF REACH OF CHILDREN

Warnings and Storage:

Ask a professional before use if pregnant or breastfeeding or if you have severe symptoms. Keep away from children. If you have a reaction to this product that is not positive, discontinue use. Store in a cool and dry place.

Warnings and Storage:

Ask a professional before use if pregnant or breastfeeding or if you have severe symptoms. Keep away from children. If you have a reaction to this product that is not positive, discontinue use. Store in a cool and dry place.

*CLAIMS BASED ON TRADITIONAL HOMEOPATHIC PRACTICE. NOT ACCEPTED MEDICAL EVIDENCE. NOT FDA EVALUATED.

This product is not intended to diagnose, treat, cure, or prevent any disease.

Entire package label